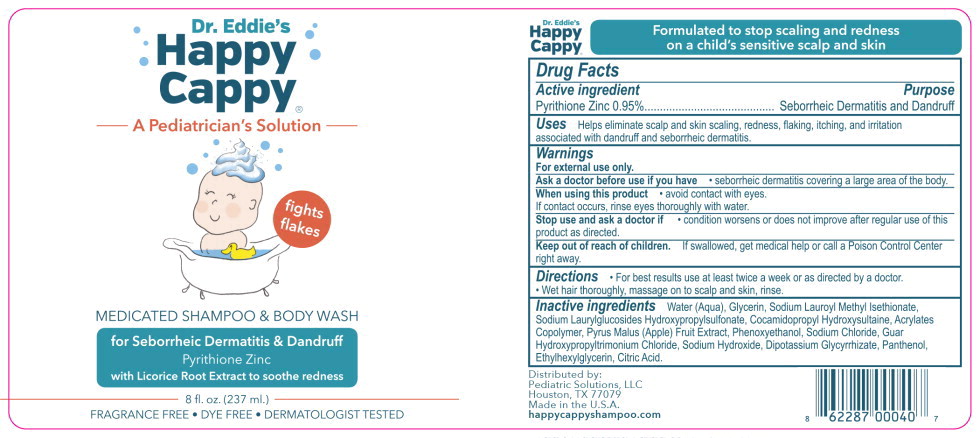 DRUG LABEL: Happy Cappy
NDC: 71566-100 | Form: SHAMPOO
Manufacturer: Pediatric Solutions, LLC
Category: otc | Type: HUMAN OTC DRUG LABEL
Date: 20251008

ACTIVE INGREDIENTS: PYRITHIONE ZINC 0.0095 g/1 mL
INACTIVE INGREDIENTS: WATER; GLYCERIN; SODIUM LAUROYL METHYL ISETHIONATE; COCAMIDOPROPYL HYDROXYSULTAINE; ACRYLIC ACID/ISOPHORONE DIISOCYANATE/PEG-27 COPOLYMER; APPLE; PHENOXYETHANOL; SODIUM CHLORIDE; GUAR HYDROXYPROPYLTRIMONIUM CHLORIDE (1.7 SUBSTITUENTS PER SACCHARIDE); SODIUM HYDROXIDE; GLYCYRRHIZINATE DIPOTASSIUM; PANTHENOL; ETHYLHEXYLGLYCERIN; CITRIC ACID MONOHYDRATE

Drug Facts

Active ingredient

Pyrithione Zinc 0.95%

Purpose

Seborrheic Dermatitis and Dandruff

Uses

Helps eliminate scalp and skin scaling, redness, flaking, itching, and irritation associated with dandruff and seborrheic dermatitis.

Warnings

For external use only.

Ask a doctor before use if you have• seborrheic dermatitis covering a large area of the body.

When using this product• avoid contact with eyes.

If contact occurs, rinse eyes thoroughly with water.

Stop use and ask a doctor if• condition worsens or does not improve after regular use of this product as directed.

Keep out of reach of children.If swallowed, get medical help or call a Poison Control Center right away.

Directions •

For best results use at least twice a week or as directed by a doctor.

- Wet hair thoroughly, massage on to scalp and skin, rinse.

Inactive ingredients

Water (Aqua), Glycerin, Sodium Lauroyl Methyl Isethionate, Sodium Laurylglucosides Hydroxypropylsulfonate, Cocamidopropyl Hydroxysultaine, Acrylates Copolymer, Pyrus Malus (Apple) Fruit Extract, Phenoxyethanol, Sodium Chloride, Guar Hydroxypropyltrimonium Chloride, Sodium Hydroxide, Dipotassium Glycyrrhizate, Panthenol, Ethylhexylglycerin, Citric Acid.

Principal Display Panel - 237 mL Bottle Label

Dr. Eddie's
Happy
Cappy ®

A Pediatrician's Solution

fights flakes

MEDICATED SHAMPOO & BODY WASH

for Seborrheic Dermatitis & Dandruff

Pyrithione Zinc

with Licorice Root Extract to soothe redness

8 fl. oz. (237 ml.)

FRAGRANCE FREE • DYE FREE • DERMATOLOGIST TESTED